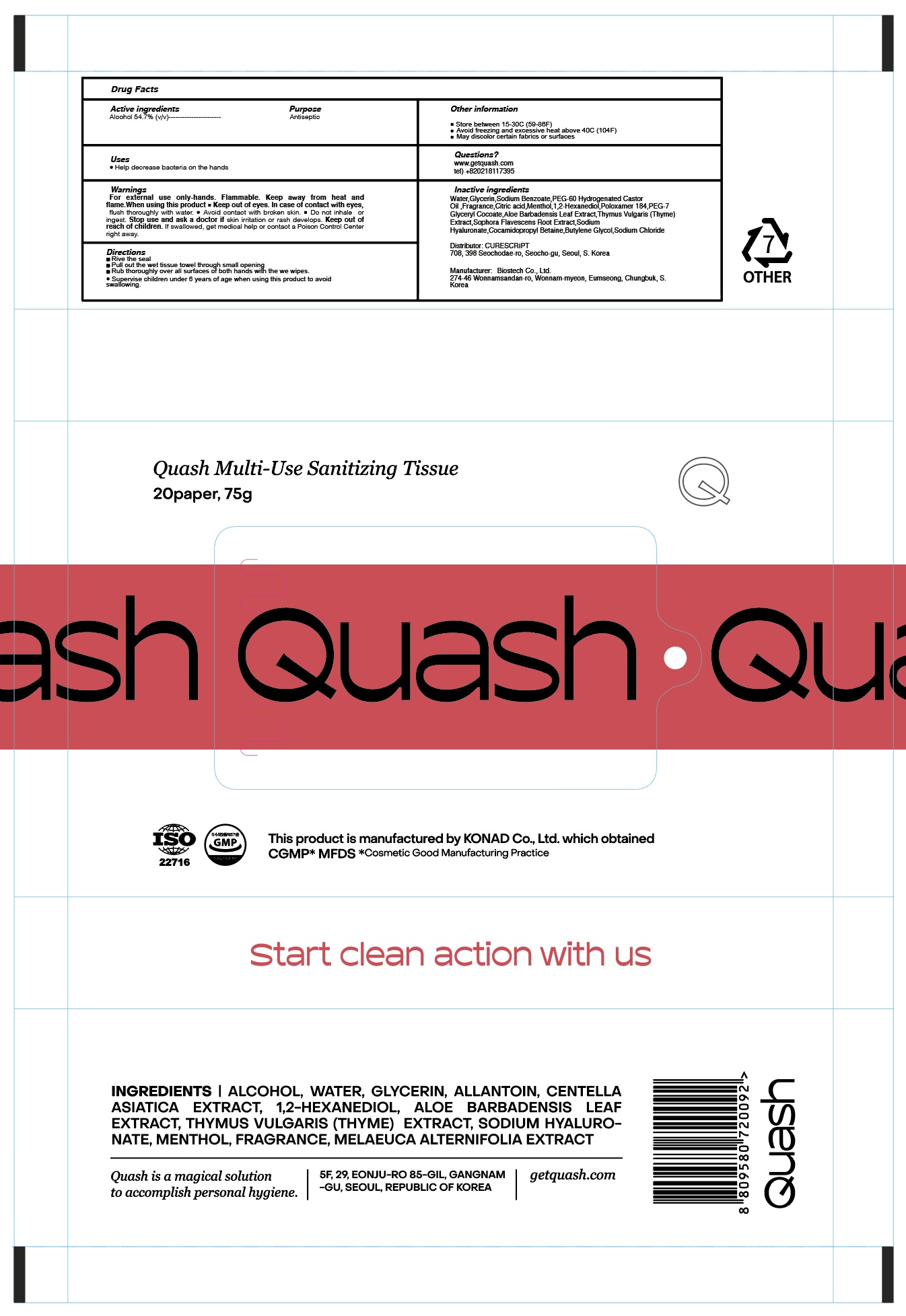 DRUG LABEL: QUASH MULTI SANITIZING TISSUE
NDC: 72265-104 | Form: CLOTH
Manufacturer: CURESCRIPT
Category: otc | Type: HUMAN OTC DRUG LABEL
Date: 20210209

ACTIVE INGREDIENTS: ALCOHOL 0.54 1/1 1
INACTIVE INGREDIENTS: Water; Glycerin; Sodium Benzoate; PEG-60 Hydrogenated Castor Oil; CITRIC ACID MONOHYDRATE; Menthol; 1,2-Hexanediol; POLOXAMER 184; PEG-7 Glyceryl Cocoate; ALOE VERA LEAF; THYME; SOPHORA FLAVESCENS ROOT; HYALURONATE SODIUM; Cocamidopropyl Betaine; Butylene Glycol; Sodium Chloride

ACTIVE INGREDIENT

Alcohol 54.7% (v/v)

INACTIVE INGREDIENTS

Water,Glycerin,Sodium Benzoate,PEG-60 Hydrogenated Castor Oil ,Fragrance,Citric acid,Menthol,1,2-Hexanediol,Poloxamer 184,PEG-7 Glyceryl Cocoate,Aloe Barbadensis Leaf Extract,Thymus Vulgaris (Thyme) Extract,Sophora Flavescens Root Extract,Sodium Hyaluronate,Cocamidopropyl Betaine,Butylene Glycol,Sodium Chloride

PURPOSE

Antiseptic

WARNINGS

For external use only-hands

Flammable. Keep away from heat and flame.

When using this product ■ Keep out of eyes. In case of contact with eyes, flush thoroughly with water. ■ Avoid contact with broken skin. ■ Do not inhale or ingest.

Stop use and ask a doctor if skin irritation or rash develops.

Keep out of reach of children. If swallowed, get medical help or contact a Poison Control Center right away.

KEEP OUT OF REACH OF CHILDREN

If swallowed, get medical help or contact a Poison Control Center right away.

Uses

■ Help decrease bacteria on the hands

Directions

■ Rive the seal
■ Pull out the wet tissue towel through small opening
■ Rub thoroughly over all surfaces of both hands with the we wipes.
■ Supervise children under 6 years of age when using this product to avoid swallowing.

Other Information

■ Store between 15-30C (59-86F)
■ Avoid freezing and excessive heat above 40C (104F)
■ May discolor certain fabrics or surfaces

QUESTIONS

www.getquash.com
tel) +820218117395